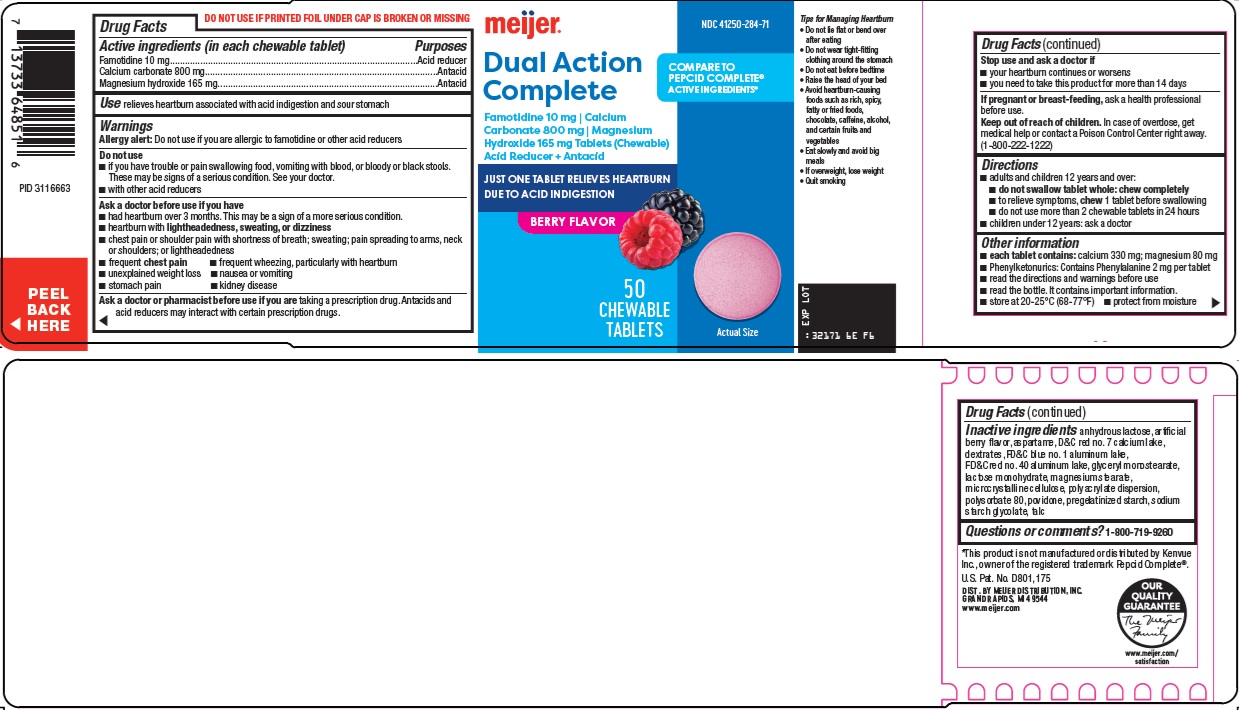 DRUG LABEL: Dual Action Complete
NDC: 41250-284 | Form: TABLET, CHEWABLE
Manufacturer: Meijer Distribution Inc
Category: otc | Type: HUMAN OTC DRUG LABEL
Date: 20260120

ACTIVE INGREDIENTS: FAMOTIDINE 10 mg/1 1; CALCIUM CARBONATE 800 mg/1 1; MAGNESIUM HYDROXIDE 165 mg/1 1
INACTIVE INGREDIENTS: ANHYDROUS LACTOSE; ASPARTAME; D&C RED NO. 7; DEXTRATES; FD&C BLUE NO. 1 ALUMINUM LAKE; FD&C RED NO. 40 ALUMINUM LAKE; GLYCERYL MONOSTEARATE; LACTOSE MONOHYDRATE; MAGNESIUM STEARATE; MICROCRYSTALLINE CELLULOSE; POLYSORBATE 80; POVIDONE, UNSPECIFIED; TALC

Meijer Distribution, Inc. Dual Action Complete Drug Facts

Active ingredients (in each chewable tablet)

Famotidine 10 mg

Calcium carbonate 800 mg

Magnesium hydroxide 165 mg

Purposes

Acid reducer

Antacid

Use

relieves heartburn associated with acid indigestion and sour stomach

Warnings

Allergy alert: Do not use if you are allergic to famotidine or other acid reducers

Do not use

- if you have trouble or pain swallowing food, vomiting with blood, or bloody or black stools. These may be signs of a serious condition. See your doctor.
- with other acid reducers

Ask a doctor before use if you have

- had heartburn over 3 months. This may be a sign of a more serious condition.
- heartburn with lightheadedness, sweating, or dizziness
- chest pain or shoulder pain with shortness of breath; sweating; pain spreading to arms, neck or shoulders; or lightheadedness
- frequent chest pain
- frequent wheezing, particularly with heartburn
- unexplained weight loss
- nausea or vomiting
- stomach pain
- kidney disease

Ask a doctor or pharmacist before use if you are

taking a prescription drug. Antacids and acid reducers may interact with certain prescription drugs.

Stop use and ask a doctor if

- your heartburn continues or worsens
- you need to take this product for more than 14 days

If pregnant or breast-feeding,

ask a health professional before use.

Keep out of reach of children.

In case of overdose, get medical help or contact a Poison Control Center right away. (1-800-222-1222)

Directions

- adults and children 12 years and over:
- do not swallow tablet whole: chew completely
- to relieve symptoms, chew 1 tablet before swallowing
- do not use more than 2 chewable tablets in 24 hours
- children under 12 years: ask a doctor

Other information

- each tablet contains: calcium 330 mg; magnesium 80 mg
- Phenylketonurics: Contains Phenylalanine 2 mg per tablet
- read the directions and warnings before use
- read the bottle. It contains important information.
- store at 20-25°C (68-77°F)
- protect from moisture

Inactive ingredients

anhydrous lactose, artificial berry flavor, aspartame, D&C red no. 7 calcium lake, dextrates, FD&C blue no. 1 aluminum lake, FD&C red no. 40 aluminum lake, glyceryl monostearate, lactose monohydrate, magnesium stearate, microcrystalline cellulose, polyacrylate dispersion, polysorbate 80, povidone, pregelatinized starch, sodium starch glycolate, talc

Questions or comments?

1-800-719-9260

Principal Display Panel

meijer®

Dual Action Complete

COMPARE TO PEPCID COMPLETE® ACTIVE INGREDIENTS

Famotidine 10 mg | Calcium

Carbonate 800 mg | Magnesium

Hydroxide 165 mg Tablets (Chewable)

Acid Reducer + Antacid

JUST ONE TABLET RELIEVES HEARTBURN DUE TO ACID INDIGESTION

BERRY FLAVOR

50 CHEWABLE TABLETS

Actual Size